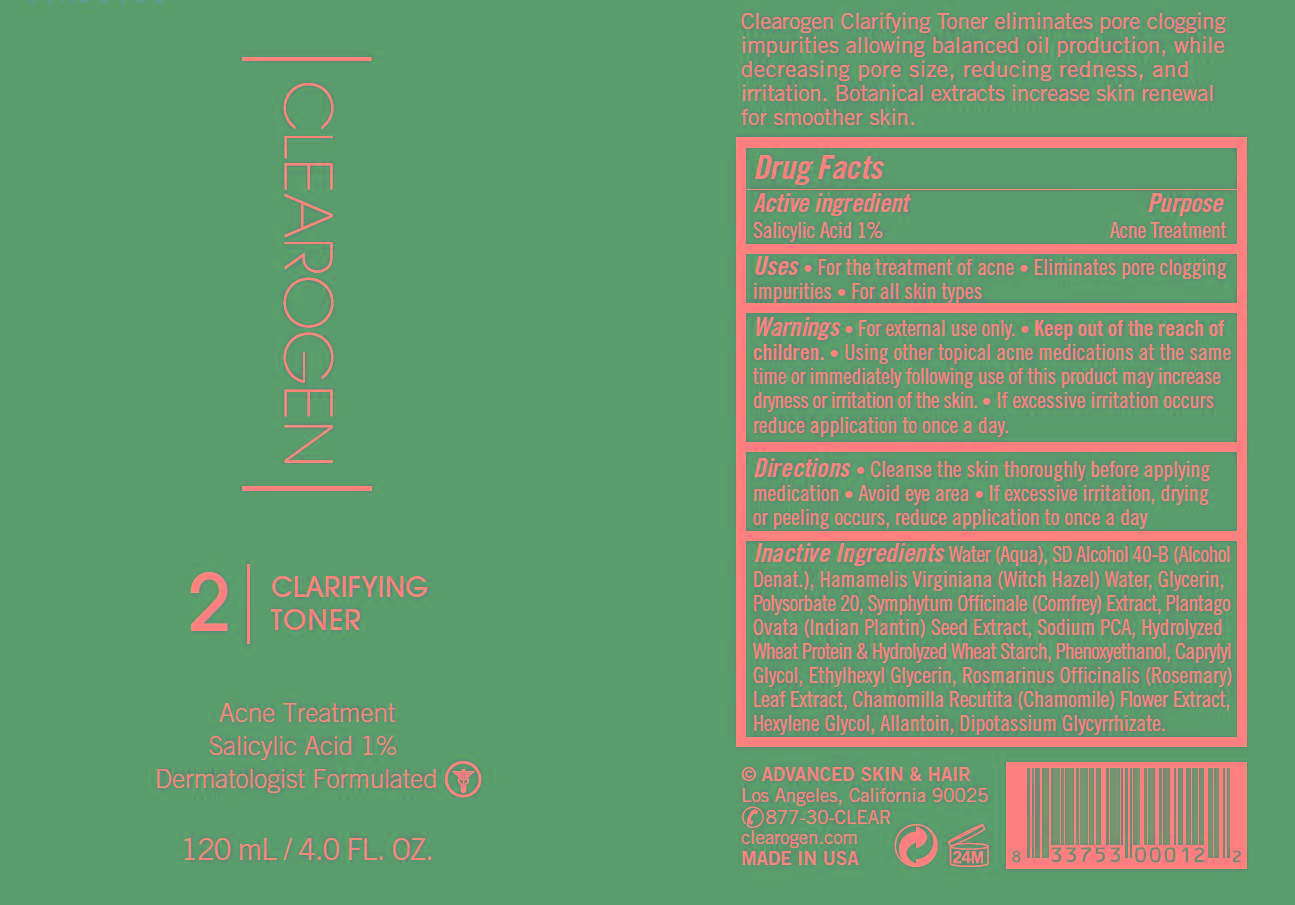 DRUG LABEL: Clarifying Toner
NDC: 62742-4167 | Form: LIQUID
Manufacturer: Allure Labs Inc
Category: otc | Type: HUMAN OTC DRUG LABEL
Date: 20181109

ACTIVE INGREDIENTS: SALICYLIC ACID 10 mg/1 mL
INACTIVE INGREDIENTS: WATER; HAMAMELIS VIRGINIANA TOP WATER; GLYCERIN; POLYSORBATE 20; COMFREY ROOT; PLANTAGO OVATA SEED; SODIUM PYRROLIDONE CARBOXYLATE; HYDROLYZED WHEAT PROTEIN (ENZYMATIC, 3000 MW); PHENOXYETHANOL ; CAPRYLYL GLYCOL; ETHYLHEXYLGLYCERIN; ROSEMARY; CHAMOMILE; HEXYLENE GLYCOL; ALLANTOIN; GLYCYRRHIZINATE DIPOTASSIUM

DRUG FACTS

Active Ingredient: Salicylic Acid 1%

Purpose: Acne Treatment

Uses:

- For the treatment of acne.
- Eliminates pore clogging impurities.
- For all skin types.

Warnings: For external use only

Keep out of the reach of children.

WHEN USING

- Using other topical acne medications at the same time or immediately following use of this product may increase dryness or irritation of the skin.
- If excessive irritation occurs reduce application to once a day.

Directions:

- Cleanse the skin thoroughly before applying medication.
- Avoid eye area.
- If excessive irritation, drying or peeling occurs, reduce application to once a day.

INACTIVE INGREDIENT

Water (Aqua), SD Alcohol 40-B (Alcohol Denat.), Hamamelis Virginiana (Witch Hazel) Water, Glycerine, Polysorbate 20, Symphytum Officinale (Comfrey) Extract, Plantago Ovata (Indian Plantin) Seed Extract, Sodium PCA, Hydrolyzed Wheat Protein, Hydrolyzed Wheat Starch, Phenoxyethanol, Caprylyl Glycol, Ethylhexyl Glycerin, Rosmarinus Officinalis (Rosemary) Leaf Extract, Chamomilla Recutita (Chamomile) Flower Extract, Hexylene Glycol, Allantoin, Dipotassium Glycyrrhizate.

PACKAGE LABEL

Advanced Skin Care

Los Angeles, California 90025

877-20-CLEAR

clearogen.com

made in USA